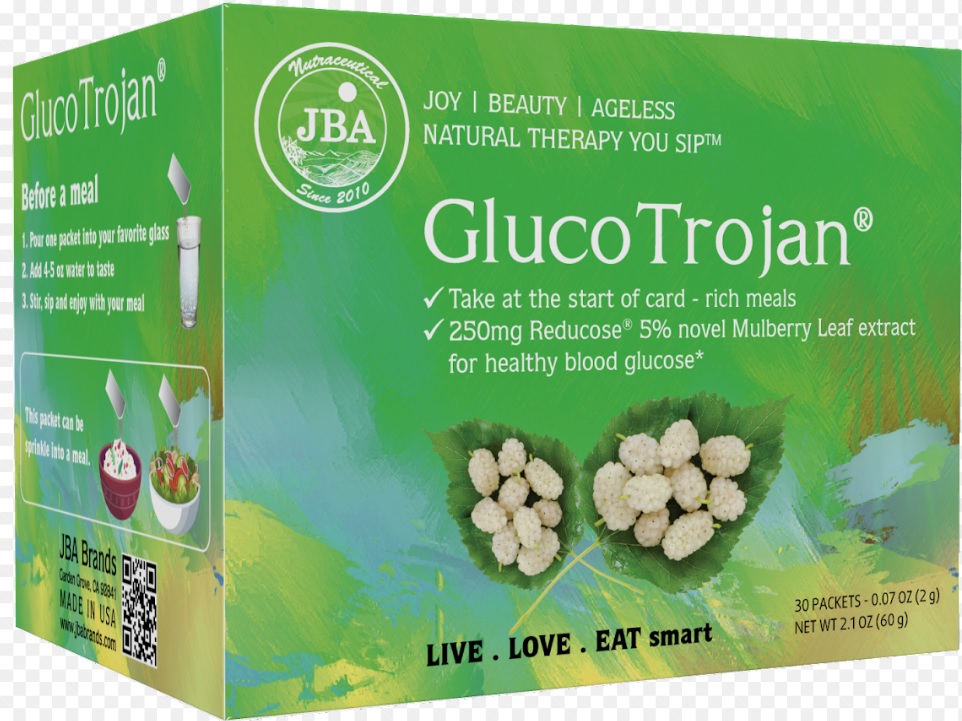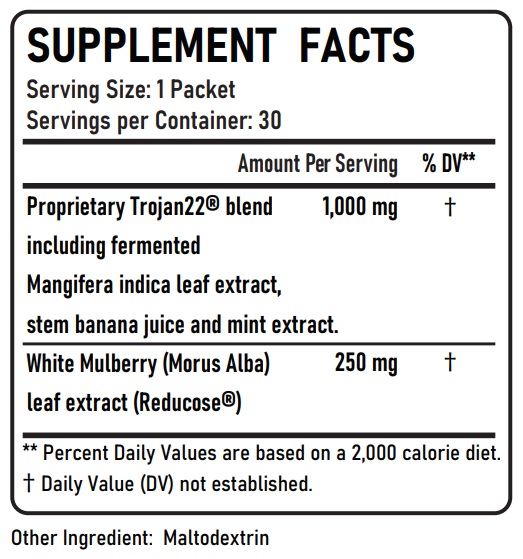 DRUG LABEL: JBA GlucoTrojan
NDC: 13411-902 | Form: POWDER
Manufacturer: Advanced Pharmaceutical Services, Inc. Dba Affordable Quality Pharmaceuticals
Category: other | Type: DIETARY SUPPLEMENT
Date: 20230220

ACTIVE INGREDIENTS: MANGO 500 mg/2 g; BANANA 500 mg/2 g; WHITE MULBERRY 250 mg/2 g
INACTIVE INGREDIENTS: MALTODEXTRIN

Identity

Dietary supplement

Warnings

- Keep out of reach of children
- Do not exceed the recommended dose
- Consult your physician prior to using this product if you are pregnant, nursing, or if you are taking blood glucose lowering medication, or have a medical condition.

Direction

Before a meal:

- Pour one packet into your favorite glass
- Add 4-5 oz water to taste
- Stir, sip and enjoy with your meal

Or

This packet can be sprinkle into a meal

Safe handling warning

Store in a cool, dry place

HEALTH CLAIM

JBA® GlucoTrojan®
For Blood Glucose Health*

- Take at the start of a carb-rich meal
- 250 mg Reducose® 5% novel Mulberry Leaf extract for healthy blood glucose*

Turning FAST sugars and other carbohydrates into SLOW ones with just one packet BEFORE MEAL
GlucoTrojan®
- Supporting healthier blood lipids*
- Healthier insulin response*
- Supporting healthier blood glucose*
- Avoid the “sugar crash”*
- Feel full for longer*
- Supporting heathy microbiome*
- Help maintain healthy BMI and weight management*
GlucoTrojan® is a meal companion powder that can be added to foods or drinks or taken as a dietary supplement to help people maintain a healthier diet.
Reducose®, an active ingredient in GlucoTrojan®, has been clinically proven in multiple studies to promote a healthier blood glucose and blood insulin response following a carbohydrate containing meal.

* These statements have not been evaluated by the Food & Drug Administration. This product is not intended to diagnose, treat, cure, or prevent any disease.